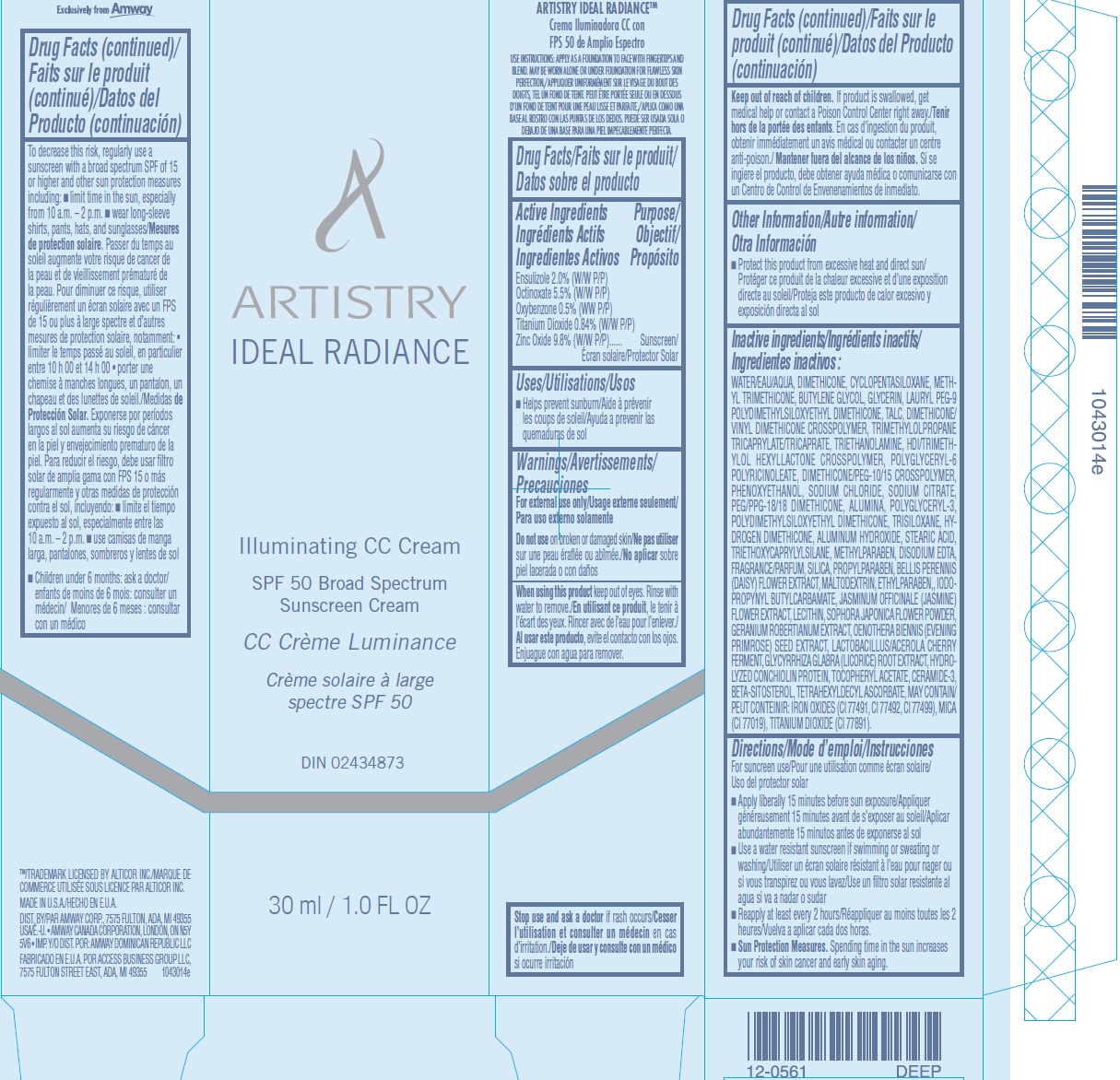 DRUG LABEL: Artistry Ideal Radiance Illuminating CC SPF 50 Broad Spectrum Sunscreen Deep
NDC: 50390-010 | Form: CREAM
Manufacturer: Amway Corp
Category: otc | Type: HUMAN OTC DRUG LABEL
Date: 20250210

ACTIVE INGREDIENTS: TITANIUM DIOXIDE 84 mg/1 mL; ZINC OXIDE 98 mg/1 mL; ENSULIZOLE 20 mg/1 mL; OCTINOXATE 55 mg/1 mL; OXYBENZONE 5 mg/1 mL
INACTIVE INGREDIENTS: WATER; DIMETHICONE; CYCLOMETHICONE 5; METHYL TRIMETHICONE; BUTYLENE GLYCOL; GLYCERIN; LAURYL PEG-9 POLYDIMETHYLSILOXYETHYL DIMETHICONE; TALC; TRIMETHYLOLPROPANE TRICAPRYLATE/TRICAPRATE; TROLAMINE; HEXAMETHYLENE DIISOCYANATE/TRIMETHYLOL HEXYLLACTONE CROSSPOLYMER; PHENOXYETHANOL; SODIUM CHLORIDE; SODIUM CITRATE; ALUMINUM HYDROXIDE; PEG/PPG-18/18 DIMETHICONE; ALUMINUM OXIDE; TRISILOXANE; STEARIC ACID; TRIETHOXYCAPRYLYLSILANE; METHYLPARABEN; EDETATE DISODIUM ANHYDROUS; SILICON DIOXIDE; PROPYLPARABEN; BELLIS PERENNIS FLOWER; MALTODEXTRIN; ETHYLPARABEN; IODOPROPYNYL BUTYLCARBAMATE; JASMINUM OFFICINALE FLOWER; GERANIUM ROBERTIANUM; EVENING PRIMROSE OIL; GLYCYRRHIZA GLABRA; .ALPHA.-TOCOPHEROL ACETATE; CERAMIDE NP; .BETA.-SITOSTEROL; TETRAHEXYLDECYL ASCORBATE

Artistry Ideal Radiance Illuminating CC SPF 50 Broad Spectrum Sunscreen Deep

Active Ingredients

Ensulizole 2.0% (W/W P/P) Octinoxate 5.5% (W/W P/P) Oxybenzone 0.5% (WW P/P) Titanium Dioxide 0.84% (W/W P/P) Zinc Oxide 9.8% (W/W P/P)

Purpose

Sunscreen

Uses

- Helps prevent sunburn

Warnings

For external use only

Do not use

on broken or damaged skin

When using this product

keep out of eyes. Rinse with water to remove.

Keep out of reach of children.

If product is swallowed, get medical help or contact a Poison Control Center right away.

Other Information

- Protect this product from excessive heat and direct sun

Inactive ingredients

WATER/EAU/AQUA, DIMETHICONE, CYCLOPENTASILOXANE, METHYL TRIMETHICONE, BUTYLENE GLYCOL, GLYCERIN, LAURYL PEG-9 POLYDIMETHYLSILOXYETHYL DIMETHICONE, TALC, DIMETHICONE/ VINYL DIMETHICONE CROSSPOLYMER, TRIMETHYLOLPROPANE TRICAPRYLATE/TRICAPRATE, TRIETHANOLAMINE, HDI/TRIMETHYLOL HEXYLLACTONE CROSSPOLYMER, POLYGLYCERYL-6 POLYRICINOLEATE, DIMETHICONE/PEG-10/15 CROSSPOLYMER, PHENOXYETHANOL, SODIUM CHLORIDE, SODIUM CITRATE, PEG/PPG-18/18 DIMETHICONE, ALUMINA, POLYGLYCERYL-3, POLYDIMETHYLSILOXYETHYL DIMETHICONE, TRISILOXANE, HYDROGEN DIMETHICONE, ALUMINUM HYDROXIDE, STEARIC ACID, TRIETHOXYCAPRYLYLSILANE, METHYLPARABEN, DISODIUM EDTA, FRAGRANCE/PARFUM, SILICA, PROPYLPARABEN, BELLIS PERENNIS (DAISY) FLOWER EXTRACT, MALTODEXTRIN, ETHYLPARABEN,, IODOPROPYNYL BUTYLCARBAMATE, JASMINUM OFFICINALE (JASMINE) FLOWER EXTRACT, LECITHIN, SOPHORA JAPONICA FLOWER POWDER, GERANIUM ROBERTIANUM EXTRACT, OENOTHERA BIENNIS (EVENING PRIMROSE) SEED EXTRACT, LACTOBACILLUS/ACEROLA CHERRY FERMENT, GLYCYRRHIZA GLABRA (LICORICE) ROOT EXTRACT, HYDROLYZED CONCHIOLIN PROTEIN, TOCOPHERYL ACETATE, CERAMIDE-3, BETA-SITOSTEROL, TETRAHEXYLDECYL ASCORBATE, MAY CONTAIN/ PEUT CONTEINIR: IRON OXIDES (CI 77491, CI 77492, CI 77499), MICA (CI 77019), TITANIUM DIOXIDE (CI 77891).

Directions

For suncreen use

- Apply liberally 15 minutes before sun exposure
- Use a water resistant sunscreen if swimming or sweating or washing
- Reapply at least every 2 hours
- Spending time in the sun increases your risk of skin cancer and early skin aging. To decrease this risk, regularly use a sunscreen with a broad spectrum SPF of 15 or higher and other sun protection measures including: Sun Protection Measures.
- limit time in the sun, especially from 10 a.m. – 2 p.m.
- wear long-sleeve shirts, pants, hats, and sunglasses
- Children under 6 months: ask a doctor